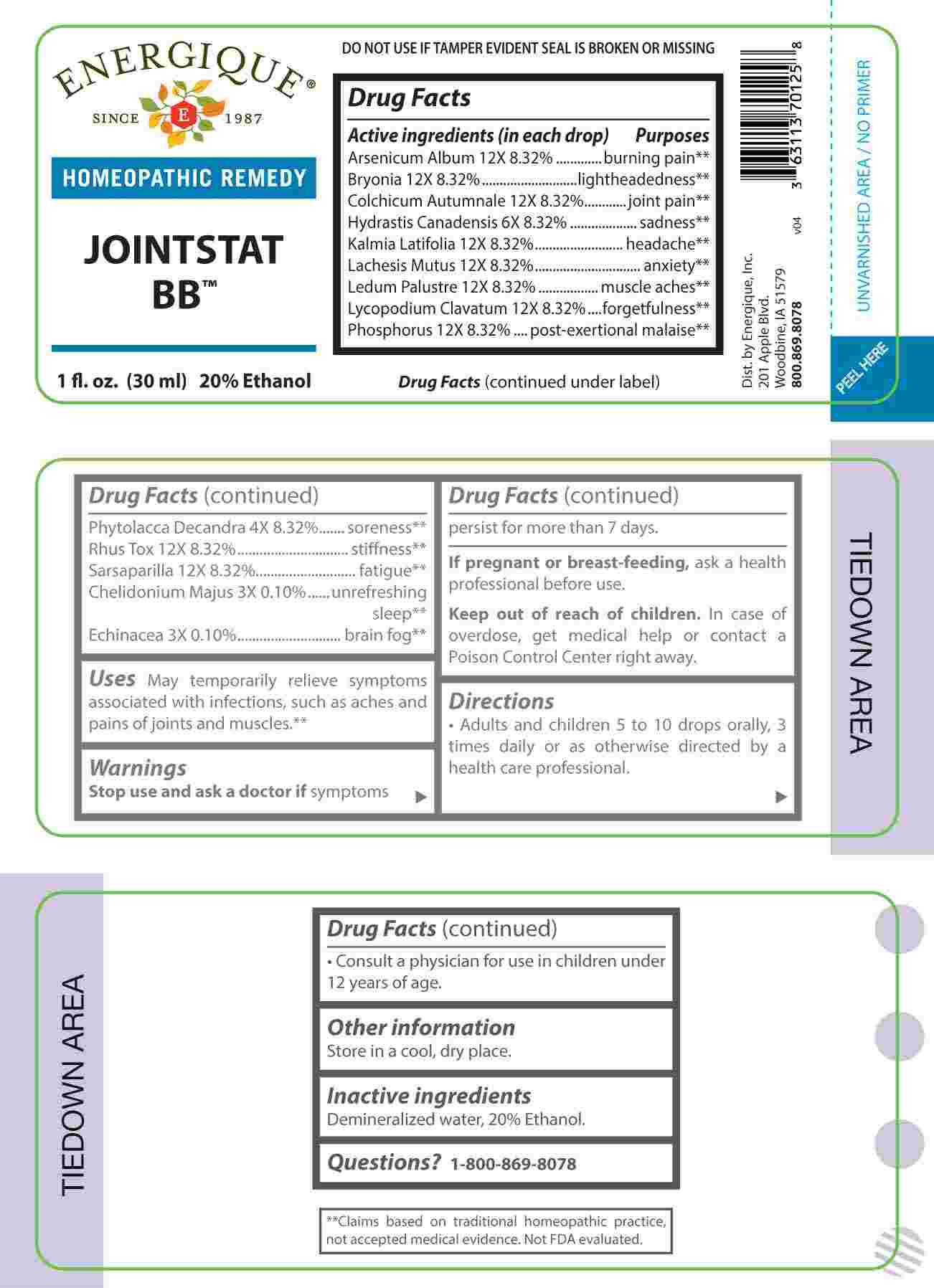 DRUG LABEL: Jointstat BB
NDC: 44911-0729 | Form: LIQUID
Manufacturer: Energique, Inc.
Category: homeopathic | Type: HUMAN OTC DRUG LABEL
Date: 20250127

ACTIVE INGREDIENTS: CHELIDONIUM MAJUS WHOLE 3 [hp_X]/1 mL; ECHINACEA ANGUSTIFOLIA WHOLE 3 [hp_X]/1 mL; PHYTOLACCA AMERICANA ROOT 4 [hp_X]/1 mL; GOLDENSEAL 6 [hp_X]/1 mL; ARSENIC TRIOXIDE 12 [hp_X]/1 mL; BRYONIA ALBA ROOT 12 [hp_X]/1 mL; COLCHICUM AUTUMNALE BULB 12 [hp_X]/1 mL; KALMIA LATIFOLIA LEAF 12 [hp_X]/1 mL; LACHESIS MUTA VENOM 12 [hp_X]/1 mL; RHODODENDRON TOMENTOSUM LEAFY TWIG 12 [hp_X]/1 mL; LYCOPODIUM CLAVATUM SPORE 12 [hp_X]/1 mL; PHOSPHORUS 12 [hp_X]/1 mL; TOXICODENDRON PUBESCENS LEAF 12 [hp_X]/1 mL; SMILAX ORNATA ROOT 12 [hp_X]/1 mL
INACTIVE INGREDIENTS: WATER; ALCOHOL

DRUG FACTS:

ACTIVE INGREDIENTS:

(in each drop): Arsenicum Album 12X 8.32%, Bryonia 12X 8.32%, Colchicum Autumnale 12X 8.32%, Hydrastis Canadensis 6X 8.32%, Kalmia Latifolia 12X 8.32%, Lachesis Mutus 12X 8.32%, Ledum Palustre 12X 8.32%, Lycopodium Clavatum 12X 8.32%, Phosphorus 12X 8.32%, Phytolacca Decandra 4X 8.32%, Rhus Tox 12X 8.32%, Chelidonium Majus 3X 0.10%, Echinacea 3X 0.10%.

PURPOSE:

Arsenicum Album – burning pain,** Bryonia - lightheadedness,** Colchicum Autumnale – joint pain,** Hydrastis Canadensis - sadness,** Kalmia Latifolia - headache,** Lachesis Mutus - anxiety,** Ledum Palustre – muscle aches,** Lycopodium Clavatum - forgetfulness,** Phosphorus – post-exertional malaise,** Phytolacca Decandra - soreness,** Rhus Tox - stiffness,** Chelidonium Majus – unrefreshing sleep,** Echinacea – brain fog**

**Claims based on traditional homeopathic practice, not accepted medical evidence. Not FDA evaluated.

USES:

May temporarily relieve symptoms associated with infections, such as aches and pains of joints and muscles.**

**Claims based on traditional homeopathic practice, not accepted medical evidence. Not FDA evaluated.

WARNINGS:

Stop use and ask a doctor if symptoms persist form more than 7 days.

If pregnant or breast-feeding, ask a health professional before use.

Keep out of reach of children. In case of overdose, get medical help or contact a Poison Control Center right away.

DO NOT USE IF TAMPER EVIDENT SEAL IS BROKEN OR MISSING

Store in a cool, dry place.

KEEP OUT OF REACH OF CHILDREN:

In case of overdose, get medical help or contact a Poison Control Center right away.

DIRECTIONS:

• Adults and children 5 to 10 drops orally, 3 times daily or as otherwise directed by a health care professional.

• Consult a physician for use in children under 12 years of age.

INACTIVE INGREDIENTS:

Demineralized water, 20% Ethanol

QUESTIONS:

Dist. by Energique, Inc.
201 Apple Blvd.
Woodbine, IA 51579

800.869.8078

PACKAGE LABEL DISPLAY:

ENERGIQUE

SINCE 1987

HOMEOPATHIC REMEDY

JOINTSTAT BB

1 fl. oz. (30 ml)